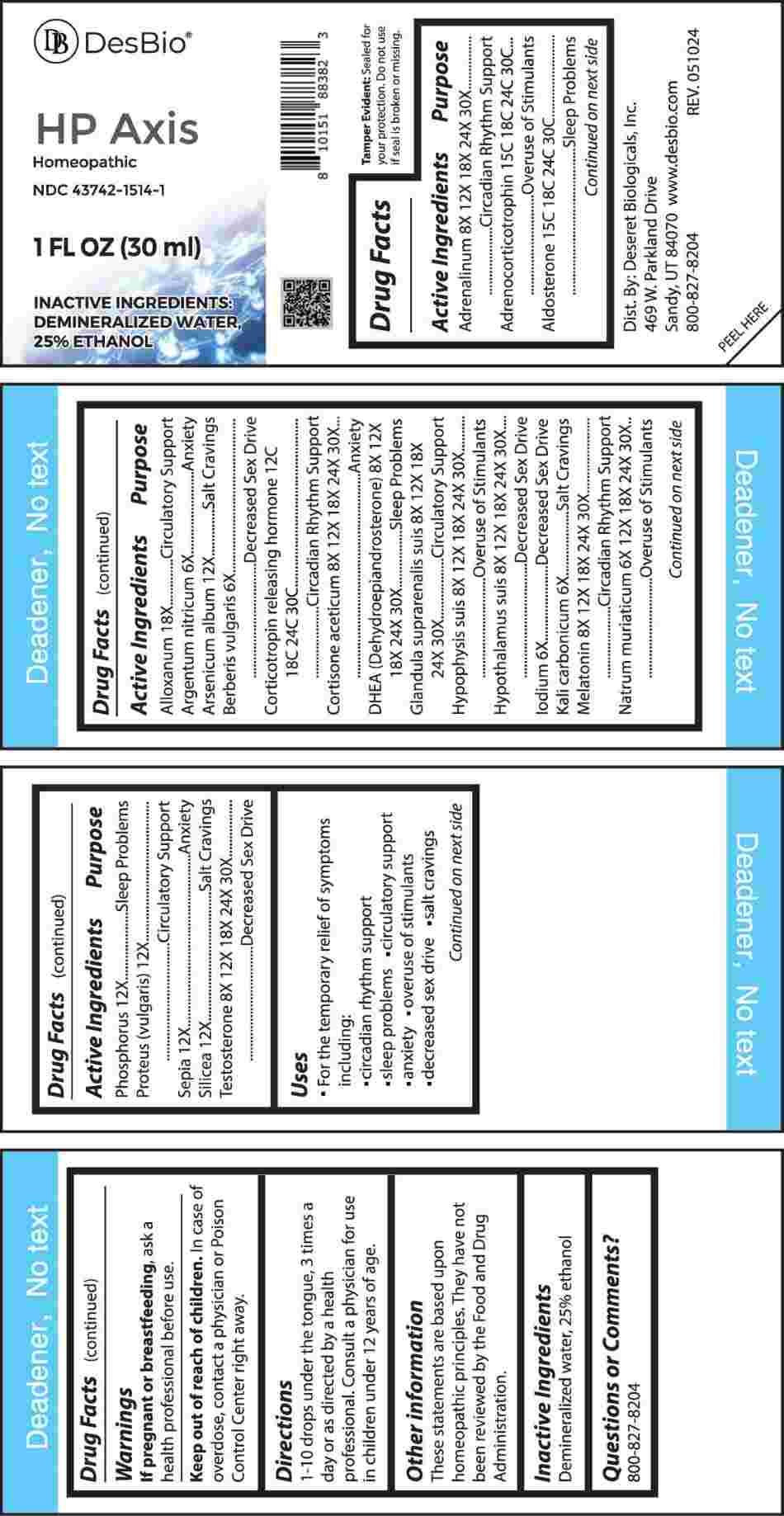 DRUG LABEL: HP Axis
NDC: 43742-1514 | Form: LIQUID
Manufacturer: Deseret Biologicals, Inc.
Category: homeopathic | Type: HUMAN OTC DRUG LABEL
Date: 20240923
DEA Schedule: CIII

ACTIVE INGREDIENTS: SILVER NITRATE 6 [hp_X]/1 mL; BERBERIS VULGARIS ROOT BARK 6 [hp_X]/1 mL; IODINE 6 [hp_X]/1 mL; POTASSIUM CARBONATE 6 [hp_X]/1 mL; SODIUM CHLORIDE 6 [hp_X]/1 mL; EPINEPHRINE 8 [hp_X]/1 mL; CORTISONE ACETATE 8 [hp_X]/1 mL; PRASTERONE 8 [hp_X]/1 mL; SUS SCROFA ADRENAL GLAND 8 [hp_X]/1 mL; SUS SCROFA PITUITARY GLAND 8 [hp_X]/1 mL; SUS SCROFA HYPOTHALAMUS 8 [hp_X]/1 mL; MELATONIN 8 [hp_X]/1 mL; TESTOSTERONE 8 [hp_X]/1 mL; ARSENIC TRIOXIDE 12 [hp_X]/1 mL; PHOSPHORUS 12 [hp_X]/1 mL; PROTEUS VULGARIS 12 [hp_X]/1 mL; SEPIA OFFICINALIS JUICE 12 [hp_X]/1 mL; SILICON DIOXIDE 12 [hp_X]/1 mL; ALLOXAN 18 [hp_X]/1 mL; CORTICORELIN 12 [hp_C]/1 mL; CORTICOTROPIN 15 [hp_C]/1 mL; ALDOSTERONE 15 [hp_C]/1 mL
INACTIVE INGREDIENTS: WATER; ALCOHOL

DRUG FACTS:

ACTIVE INGREDIENTS:

Adrenalinum 8X, 12X, 18X, 24X, 30X, Adrenocorticotrophin 15C, 18C, 24C, 30C, Aldosterone 15C, 18C, 24C, 30C, Alloxanum 18X, Argentum Nitricum 6X, Arsenicum Album 12X, Berberis Vulgaris 6X, Corticotropin Releasing Hormone 12C, 18C, 24C, 30C, Cortisone Aceticum 8X, 12X, 18X, 24X, 30X, DHEA (Dehydroepiandrosterone) 8X, 12X, 18X, 24X, 30X, Glandula Suprarenalis Suis 8X, 12X, 18X, 24X, 30X, Hypophysis Suis 8X, 12X, 18X, 24X, 30X, Hypothalamus Suis 8X, 12X, 18X, 24X, 30X, Iodium 6X, Kali Carbonicum 6X, Melatonin 8X, 12X, 18X, 24X, 30X, Natrum Muriaticum 6X, 12X, 18X, 24X, 30X, Phosphorus 12X, Proteus (Vulgaris) 12X, Sepia 12X, Silicea 12X, Testosterone 8X, 12X, 18X, 24X, 30X.

PURPOSE:

Adrenalinum – Circadian Rhythm Support, Adrenocorticotrophin – Overuse of Stimulants, Aldosterone – Sleep Problems, Alloxanum – Circulatory Support, Argentum Nitricum - Anxiety, Arsenicum Album – Salt Cravings, Berberis Vulgaris – Decreased Sex Drive, Corticotropin Releasing Hormone – Circadian Rhythm Support, Cortisone Aceticum - Anxiety, DHEA (Dehydroepiandrosterone) – Sleep Problems, Glandula Suprarenalis Suis - Circulatory Support, Hypophysis Suis – Overuse of Stimulants, Hypothalamus Suis – Decreased Sex Drive, Iodium – Decreased Sex Drive, Kali Carbonicum – Salt Cravings, Melatonin – Circadian Rhythm Support, Natrum Muriaticum – Overuse of Stimulants, Phosphorus – Sleep Problems, Proteus (Vulgaris) – Circulatory Support, Sepia - Anxiety, Silicea – Salt Cravings, Testosterone – Decreased Sex Drive

USES:

• For the temporary relief of symptoms including:

• circadian rhythm support • sleep problems • circulatory support

• anxiety • overuse of stimulants • decreased sex drive • salt cravings

These statements are based upon homeopathic principles. They have not been reviewed by the Food and Drug Administration.

WARNINGS:

If pregnant or breast-feeding, ask a health professional before use.

Keep out of reach of children. In case of overdose, contact a physician or Poison Control Center right away.

Tamper Evident: Sealed for your protection. Do not use if seal is broken or missing.

KEEP OUT OF REACH OF CHILDREN:

In case of overdose, contact a physician or Poison Control Center right away.

DIRECTIONS:

1-10 drops under the tongue, 3 times a day or as directed by a health professional. Consult a physician for use in children under 12 years of age.

INACTIVE INGREDIENTS:

Demineralized water, 25% ethanol

QUESTIONS:

Dist. By: Deseret Biologicals, Inc.
469 W. Parkland Drive
Sandy, UT 84070

www.desbio.com

800-827-8204

PACKAGE LABEL DISPLAY:

Des Bio

HP Axis

Homeopathic

NDC 43742-1514-1

1 FL OZ (30 ml)